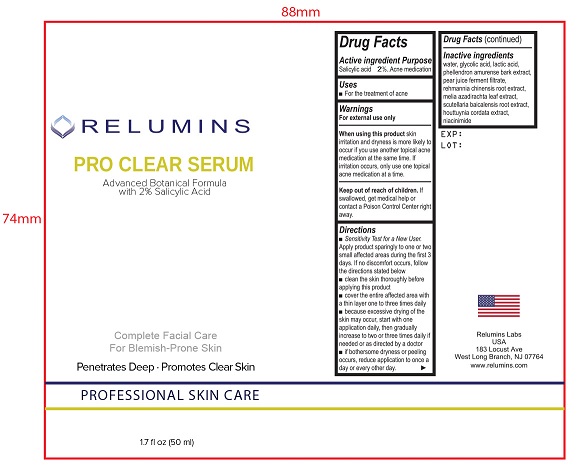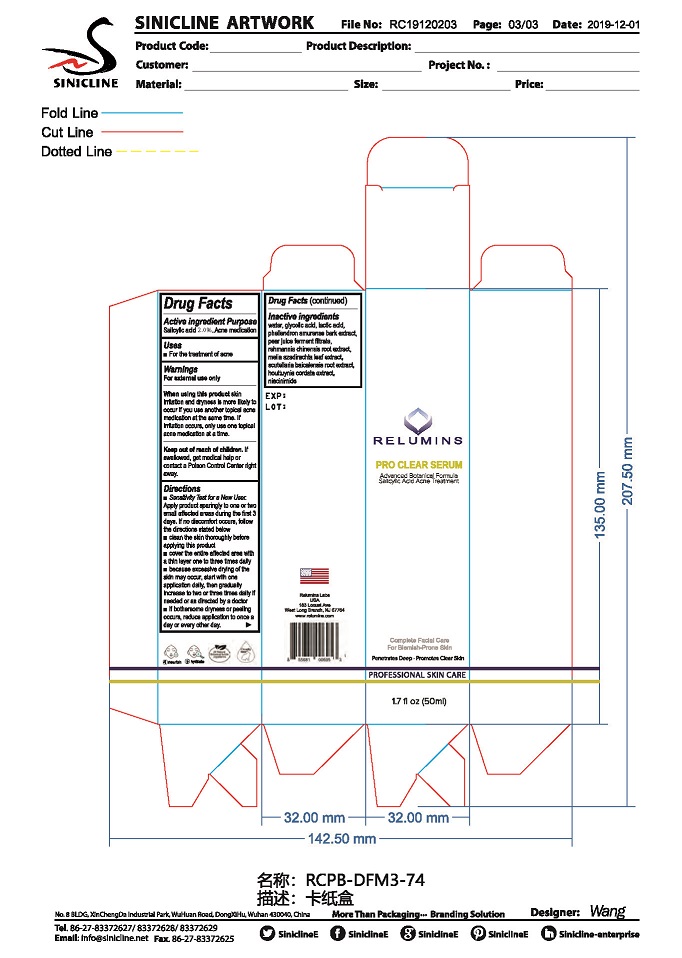 DRUG LABEL: Pro Clear Serum
NDC: 79061-040 | Form: LIQUID
Manufacturer: Relumins Labs LLC
Category: otc | Type: HUMAN OTC DRUG LABEL
Date: 20210701

ACTIVE INGREDIENTS: SALICYLIC ACID 2 mg/100 mL
INACTIVE INGREDIENTS: WATER; GLYCOLIC ACID; LACTIC ACID; NIACINAMIDE; PHELLODENDRON AMURENSE BARK; PEAR JUICE; REHMANNIA GLUTINOSA ROOT; SCUTELLARIA BAICALENSIS ROOT; HOUTTUYNIA CORDATA FLOWERING TOP; AZADIRACHTA INDICA LEAF

Relumins Pro Clear Serum: Advanced Botanical Formula with 2% Salicyclic Acid

Active ingredient

Salicylic acid 2.0%

Purpose

- Acne medication

Uses

- For the treatment of acne

Warnings

For external use only

When using this product

- skin irritation and dryness is more likely to occur if you use another topical acne medication at the same time. If irritation occurs, only use one topical acne medication at a time.

Keep out of reach of children.

If swallowed, get medical help or contact a Poison Control Center right away.

Directions

- Sensitivity Test for a New User. Apply product sparingly to one or two small affected areas during the first 3 days. If no discomfort occurs, follow the directions stated below
- clean the skin thoroughly before applying this product
- cover the entire affected area with a layer one to three times daily
- because excessive drying of the skin may occur, start with one application daily, then gradually increase to two or three times daily if needed or as directed by a doctor
- if bothersome dryness or peeling occurs, reduce application to once a day or every other day

Inactive ingredients

water, glycolic acid, lactic acid, phellendron amurense bark extract, pear juice ferment filtrate, rehmannia chinensis root extract, melia azadirachta leaf extract, scutellaria baicalensis root extract, houttuynia cordata extract, niacinimide

Bottle Label

RELUMINS

PRO CLEAR SERUM

Advanced Botanical Formula with 2% Salicylic Acid

Complete Facial Care For Blemish-Prone Skin

Penetrates Deep • Promotes Clear Skin

PROFESSIONAL SKIN CARE

1.7 fl oz (50 ml)

EXP:

LOT:

Relumins Labs

USA

183 Locust Ave

West Long Branch, NJ 07764

www.relumins.com

Carton Label

RELUMINS

PRO CLEAR FOAM

Advanced Botanical Formula with 2% Salicylic Acid

Complete Facial Care For Blemish-Prone Skin

Penetrates Deep • Promotes Clear Skin

PROFESSIONAL SKIN CARE

1.7 fl oz (50 ml)

EXP:

LOT:

Relumins Labs

USA

183 Locust Ave

West Long Branch, NJ 07764

www.relumins.com